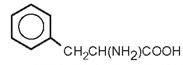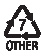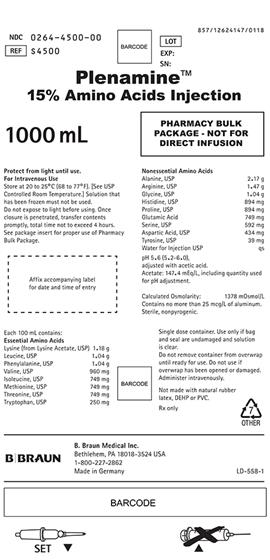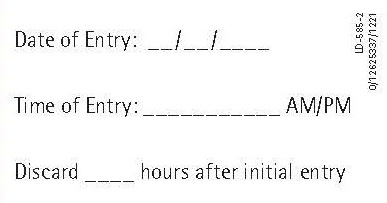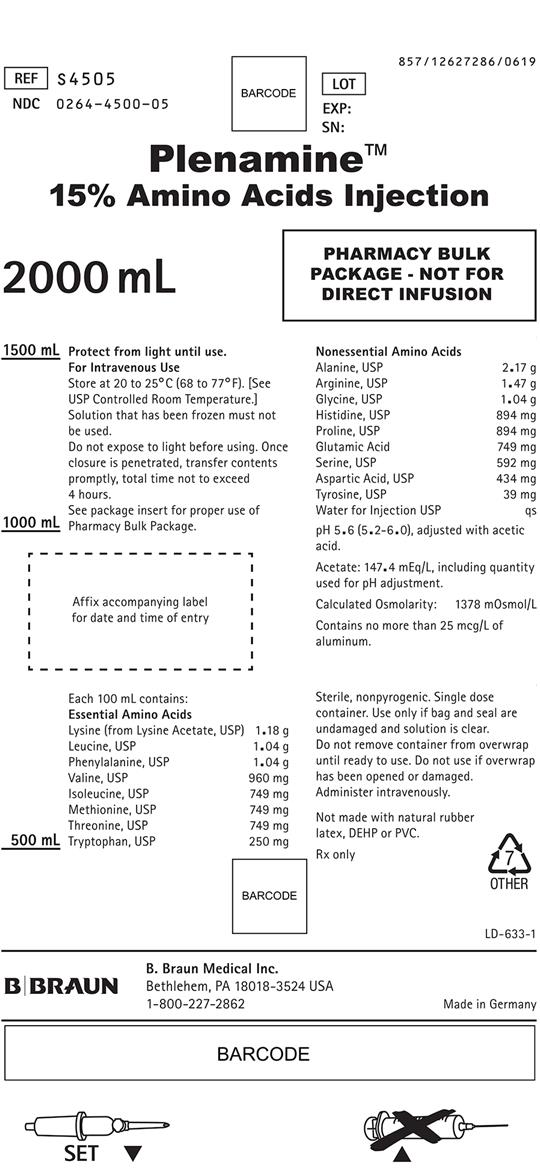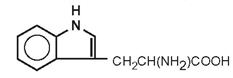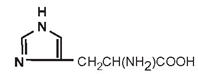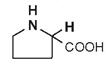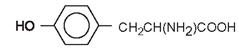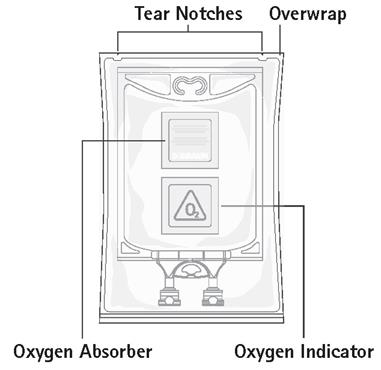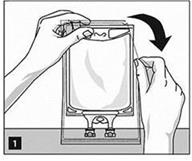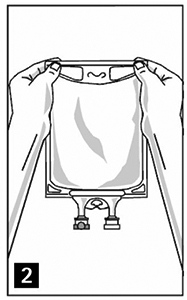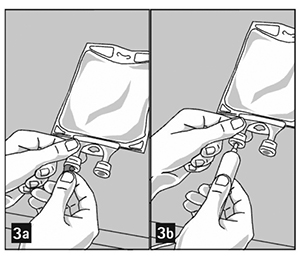 DRUG LABEL: Plenamine
NDC: 0264-4500 | Form: SOLUTION
Manufacturer: B. Braun Medical Inc.
Category: prescription | Type: HUMAN PRESCRIPTION DRUG LABEL
Date: 20230421

ACTIVE INGREDIENTS: LYSINE ACETATE 1.18 g/100 mL; LEUCINE 1.04 g/100 mL; PHENYLALANINE 1.04 g/100 mL; VALINE 960 mg/100 mL; ISOLEUCINE 749 mg/100 mL; METHIONINE 749 mg/100 mL; THREONINE 749 mg/100 mL; TRYPTOPHAN 250 mg/100 mL; ALANINE 2.17 g/100 mL; ARGININE 1.47 g/100 mL; GLYCINE 1.04 g/100 mL; HISTIDINE 894 mg/100 mL; PROLINE 894 mg/100 mL; GLUTAMIC ACID 749 mg/100 mL; SERINE 592 mg/100 mL; ASPARTIC ACID 434 mg/100 mL; TYROSINE 39 mg/100 mL
INACTIVE INGREDIENTS: WATER; ACETIC ACID

Plenamine™
15% Amino Acids Injection

Package Insert

PHARMACY BULK PACKAGE
NOT FOR DIRECT INFUSION

Protect from light until use.

DESCRIPTION

Plenamine™ 15% Amino Acids Injection in a Pharmacy Bulk Package is a sterile, clear, nonpyrogenic solution of essential and nonessential amino acids for intravenous infusion in parenteral nutrition following appropriate dilution.

Plenamine™ 15% in a Pharmacy Bulk Package is not for direct infusion. It is a sterile dosage form which contains several single doses for use in a pharmacy admixture program in the preparation of intravenous parenteral fluids.

Each 100 mL contains:

Essential Amino Acids
Lysine (from Lysine Acetate, USP) | 1.18 | g
Leucine, USP | 1.04 | g
Phenylalanine, USP | 1.04 | g
Valine, USP | 960 | mg
Isoleucine, USP | 749 | mg
Methionine, USP | 749 | mg
Threonine, USP | 749 | mg
Tryptophan, USP | 250 | mg
Nonessential Amino Acids
Alanine, USP | 2.17 | g
Arginine, USP | 1.47 | g
Glycine, USP | 1.04 | g
Histidine, USP | 894 | mg
Proline, USP | 894 | mg
Glutamic Acid | 749 | mg
Serine, USP | 592 | mg
Aspartic Acid, USP | 434 | mg
Tyrosine, USP | 39 | mg
Water for Injection, USP |  | qs
Essential Amino Acids | 6.7 | g
Nonessential Amino Acids | 8.3 | g
Total Amino Acids | 15.0 | g
Total Nitrogen | 2.37 | g
Acetate [Acetate from Lysine Acetate, USP and acetic acid used for pH adjustment.] | 147.4 | mEq/L
Osmolarity (calculated) | 1378 | mOsmol/L
pH 5.6 (5.2–6.0)

The formulas for the individual amino acids are as follows:

Essential Amino Acids
Lysine Acetate | H2N(CH2)4CH(NH2)COOH•CH3COOH
Leucine | (CH3)2CHCH2CH(NH2)COOH
Phenylalanine
Valine | (CH3)2CHCH(NH2)COOH
Isoleucine | CH3CH2CH(CH3)CH(NH2)COOH
Methionine | CH3S(CH2)2CH(NH2)COOH
Threonine | CH3CH(OH)CH(NH2)COOH
Tryptophan
Nonessential Amino Acids
Alanine | CH3CH(NH2)COOH
Arginine | H2NC(NH)NH(CH2)3CH(NH2)COOH
Glycine | H2NCH2COOH
Histidine
Proline
Glutamic Acid | HOOC(CH2)2CH(NH2)COOH
Serine | HOCH2CH(NH2)COOH
Aspartic Acid | HOOCCH2CH(NH2)COOH
Tyrosine

CLINICAL PHARMACOLOGY

Plenamine™ 15% Amino Acids Injection provides seventeen crystalline amino acids. This completely utilizable substrate promotes protein synthesis and wound healing and reduces the rate of protein catabolism.

A. Total Parenteral Nutrition (Central Infusion)

When enteral feeding is inadvisable, Plenamine™ 15% given by central venous infusion in combination with energy sources, vitamins, trace elements and electrolytes, will completely satisfy the requirements for weight maintenance or weight gain, depending upon the dose selected. The energy component in parenteral nutrition by central infusion may be derived solely from dextrose or may be provided by a combination of dextrose and intravenous fat emulsion. The addition of intravenous fat emulsion provides essential fatty acids and permits a dietary balance of fat and carbohydrate, at the same time offering the option of reducing the dextrose load and/or increasing the total caloric input. An adequate energy supply is essential for optimal utilization of amino acids.

B. Total Parenteral Nutrition (Peripheral Infusion)

Plenamine™ 15% can also be administered as part of a total parenteral nutrition program by peripheral vein when the enteral route is inadvisable and use of the central venous catheter is contraindicated.

Reduction of protein loss can be achieved by use of diluted Plenamine™ 15% in combination with dextrose or with dextrose and intravenous fat emulsion by peripheral infusion. Complete peripheral intravenous nutrition can be achieved in patients with low caloric requirements by a Plenamine™ 15% dextrose-fat regimen.

INDICATIONS AND USAGE

Plenamine™ 15% is indicated as an amino acid (nitrogen) source in parenteral nutrition regimens. This use is appropriate when the enteral route is inadvisable, inadequate or not possible, as when:

— Gastrointestinal absorption is impaired by obstruction, inflammatory disease or its complications, or antineoplastic therapy;

— Bowel rest is needed because of gastrointestinal surgery or its complications such as ileus, fistulae or anastomotic leaks;

— Tube feeding methods alone cannot provide adequate nutrition.

CONTRAINDICATIONS

This solution should not be used in patients in hepatic coma, severe renal failure, metabolic disorders involving impaired nitrogen utilization or hypersensitivity to one or more amino acids.

WARNINGS

Administration of amino acids solutions at excessive rates or to patients with hepatic insufficiency may result in plasma amino acid imbalances, hyperammonemia, prerenal azotemia, stupor and coma. Conservative doses of amino acids should be given to these patients, dictated by the nutritional status of the patient. Should symptoms of hyperammonemia develop, amino acid administration should be discontinued and the patient's clinical status re-evaluated.

WARNING: This product contains aluminum that may be toxic. Aluminum may reach toxic levels with prolonged parenteral administration if kidney function is impaired. Premature neonates are particularly at risk because their kidneys are immature, and they require large amounts of calcium and phosphate solutions, which contain aluminum.

Research indicates that patients with impaired kidney function, including premature neonates, who receive parenteral levels of aluminum at greater than 4 to 5 mcg/kg/day accumulate aluminum at levels associated with central nervous system and bone toxicity. Tissue loading may occur at even lower rates of administration.

PRECAUTIONS

A. General

It is essential to provide adequate calories concurrently if parenterally administered amino acids are to be retained by the body and utilized for protein synthesis.

The administration of Plenamine™ 15% Amino Acids Injection as part of total parenteral nutrition (TPN) with large volumes of hyperosmotic fluids requires periodic monitoring of the patient for signs of hyperosmolarity, hyperglycemia, glycosuria and hypertriglyceridemia.

During parenteral nutrition with concentrated dextrose and amino acids solutions, essential fatty acid deficiency syndrome may develop but may not be clinically apparent. Early demonstration of this condition can only be accomplished by gas liquid chromatographic analysis of plasma lipids. The syndrome may be prevented or corrected by appropriate treatment with intravenous fat emulsions.

For complete nutritional support, TPN regimens must also include multiple vitamins and trace elements. Potentially incompatible ions such as calcium and phosphate may be added to alternate infusate bottles to avoid precipitation. Although the metabolizable acetate ion in Plenamine™ 15% diminishes the risk of acidosis, the physician must be alert to the potential appearance of this disorder.

Initiation and termination of infusions of TPN fluids must be gradual to permit adjustment of endogenous insulin release.

Undiluted Plenamine™ 15% should not be administered peripherally. When administered centrally, it should be diluted with appropriate diluents, e.g., dextrose, electrolytes and other nutrient components, to at least half strength. (See DOSAGE AND ADMINISTRATION.)

Caution against volume overload should be exercised.

Drug product contains no more than 25 mcg/L of aluminum.

B. Laboratory Tests

Infusion of Plenamine™ 15% without concomitant infusion of an adequate number of non-protein calories may result in elevated BUN. Monitoring of BUN is required and the balance between Plenamine™ 15% and the calorie source may require adjustment. Frequent clinical evaluations and laboratory determinations are required to prevent the complications which may occur during the administration of solutions used in TPN. Laboratory tests should include blood glucose, serum electrolytes, liver and kidney function, serum osmolarity, blood ammonia, serum protein, pH, hematocrit, WBC and urinary glucose. When Plenamine™ 15% is combined with electrolytes, care should be used in administering this solution to patients with congestive heart failure, renal failure, edema, adrenal hyperactivity, acid-base imbalance and those receiving diuretics or antihypertensive therapy. Total volume infused should be closely monitored. Serum electrolytes should be monitored daily in these patients.

C. Carcinogenesis, Mutagenesis, Impairment of Fertility

Studies with Plenamine™ 15% have not been performed to evaluate carcinogenic potential, mutagenic potential, or effects on fertility.

D. Pregnancy Category C

Animal reproduction studies have not been conducted with Plenamine™ 15%. It is also not known whether Plenamine™ 15% can cause fetal harm when administered to a pregnant woman or can affect reproduction capacity. Plenamine™ 15% should be given to a pregnant woman only if clearly needed.

E. Nursing Mothers

Caution should be exercised when Plenamine™ 15% is administered to a nursing woman.

F. Pediatric Use

Safety and effectiveness of Plenamine™ 15% Amino Acids Injection in pediatric patients have not been established by adequate and well-controlled studies. However, the use of amino acids injections in pediatric patients as an adjunct in the offsetting of nitrogen loss or in the treatment of negative nitrogen balance is referenced in the medical literature.

G. Special Precautions for Central Infusion

TPN delivered by indwelling catheter through a central or large peripheral vein is a special technique requiring a team effort by physician, nurse and pharmacist. The responsibility for administering this therapy should be confined to those trained in the procedures and alert to signs of complications. Complications known to occur from the placement of central venous catheter are pneumothorax, hemothorax, hydrothorax, artery puncture and transection, injury to the brachial plexus, malposition of the catheter, formation of arteriovenous fistula, phlebitis, thrombosis, and air/catheter emboli. The risk of sepsis is present during intravenous therapy, especially when using central venous catheters for prolonged periods. It is imperative that the preparation of admixtures and the placement and care of the catheters be accomplished under controlled aseptic conditions.

H. Admixtures

Admixtures should be prepared under a laminar flow hood using aseptic technique.

Admixtures should be stored under refrigeration and must be administered within 24 hours after removal from refrigerator.

Filters of less than 1.2 micron pore size must not be used with admixtures containing lipid emulsion.

I. Use only if bag and seal are undamaged and solution is clear.

IT IS ESSENTIAL THAT A CAREFULLY PREPARED PROTOCOL, BASED ON CURRENT MEDICAL PRACTICES, BE FOLLOWED, PREFERABLY BY AN EXPERIENCED TEAM.

ADVERSE REACTIONS

(See WARNINGS, PRECAUTIONS and Special Precautions for Central Infusion.)

OVERDOSAGE

In the event of overhydration or solute overload, re-evaluate the patient and institute appropriate corrective measures. (See WARNINGS and PRECAUTIONS.)

DOSAGE AND ADMINISTRATION

The appropriate daily dose of amino acids to be used with dextrose or with dextrose and intravenous fat emulsion will depend upon the metabolic status and clinical response of the patient as therapy proceeds. Doses which achieve nitrogen equilibrium or positive balance are the most desirable. The dosage on the first day should be approximately half the anticipated optimal dosage and should be increased gradually to minimize glycosuria; similarly, withdrawal should be accomplished gradually to avoid rebound hypoglycemia.

Fat emulsion coadministration should be considered when prolonged (more than 5 days) parenteral nutrition is required in order to prevent essential fatty acid deficiency (EFAD). Serum lipids should be monitored for evidence of EFAD in patients maintained on fat free TPN.

The amount administered is dosed on the basis of amino acids/kg of body weight/day. In general, two to three g/kg of body weight for neonates and infants with adequate calories are sufficient to satisfy protein needs and promote positive nitrogen balance. In pediatric patients, the final solution should not exceed twice normal serum osmolarity (718 mOsmol/L).

DIRECTIONS FOR PROPER USE OF PHARMACY BULK PACKAGE

Plenamine™ 15% in a Pharmacy Bulk Package is not intended for direct infusion. The container closure may be penetrated only once using a suitable unvented sterile transfer device or dispensing set which allows measured dispensing of the contents. The Pharmacy Bulk Package is to be used only in a suitable work area such as a laminar flow hood (or an equivalent clean air compounding area). Once the closure is penetrated, the contents should be dispensed as soon as possible; the transfer of contents must be completed within 4 hours of closure entry. The bag may be stored at room temperature (25°C) after the closure has been entered.

When using Plenamine™ 15% in patients with a need for fluid volume restriction, it can be diluted as follows:

 | Volume | Amount | Final Concentration
Plenamine™ 15% | 500 mL | 75 g | 7.5%
Dextrose 70% | 250 mL | 175 g | 17.5%
Intralipid® 20% | 250 mL | 50 g | 5.0%

This will provide 1395 kilocalories (kcal) per 1000 mL of admixture with a ratio of 118 non-protein calories per gram of nitrogen and an osmolarity of 1559 mOsmol/L.

In patients where the need for fluid restriction is not so marked, either of the following regimens may be used dependent upon the energy needs of the patient.

 | Volume | Amount | Final Concentration
Plenamine™ 15% | 500 mL | 75 g | 3.75%
Dextrose 50% | 1000 mL | 500 g | 25%
Intralipid® 20% | 500 mL | 100 g | 5%

This will provide 1500 kcal per 1000 mL of admixture with a ratio of 228 non-protein calories per gram of nitrogen and an osmolarity of 1631 mOsmol/L.

 | Volume | Amount | Final Concentration
Plenamine™ 15% | 500 mL | 75 g | 3.75%
Dextrose 30% | 1000 mL | 300 g | 15%
Intralipid® 10% | 500 mL | 50 g | 2.5%

This will provide 935 kcal per 1000 mL of admixture with a ratio of 158 non-protein calories per gram of nitrogen and an osmolarity of 1126 mOsmol/L.

A. Total Parenteral Nutrition (Central Infusion)

In unstressed adult patients with no unusual nitrogen losses, a minimum dosage of 0.1 gram nitrogen (4.2 mL of Plenamine™ 15%) plus 4.4 grams (15 calories) of dextrose per kilogram of body weight per day are required to achieve nitrogen balance and weight stability. Intravenous fat emulsion may be used as a partial substitute for dextrose. This regimen provides a ratio of 150 non-protein calories per gram of nitrogen.

For patients stressed by surgery, trauma or sepsis, and those with unusual nitrogen losses, the dosage required for maintenance may be as high as 0.3 to 0.4 grams of nitrogen (13 to 17 mL Plenamine™ 15%) per kilogram of body weight per day, with proportionate increases in non-protein calories. Periodic assessment of nitrogen balance of the individual patient is the best indicator of proper dosage. Volume overload and glycosuria may be encountered at high dosage, and nitrogen balance may not be achieved in extremely hypermetabolic patients under these constraints. Concomitant insulin administration may be required to minimize glycosuria. Daily laboratory monitoring is essential.

Use of an infusion pump is advisable to maintain a steady infusion rate during central venous infusion.

B. Peripheral Nutrition

In patients for whom central venous catheterization is not advisable, protein catabolism can be reduced by peripheral use of diluted Plenamine™ 15% plus non-protein calorie sources. Dilution of 250 mL Plenamine™ 15% in 750 mL of 10% dextrose will reduce the osmolarity to a level (724 mOsmol/L) which is more favorable to the maintenance of the integrity of the walls of the veins. Intravenous fat emulsion can be infused separately or simultaneously; if infused simultaneously the fat emulsion will provide a dilution effect upon the osmolarity while increasing the energy supply.

Parenteral drug products should be inspected visually for particulate matter and discoloration prior to administration, whenever solution and container permit.

To reduce the risk of bacterial contamination, all intravenous administration sets should be replaced at least every 24 hours. Usage of admixtures must be initiated within 24 hours after mixing. If storage is necessary during this 24 hour period, admixtures must be refrigerated and completely used within 24 hours of beginning administration.

HOW SUPPLIED

Plenamine™ 15% Amino Acids Injection is supplied sterile and nonpyrogenic in flexible plastic bags, Pharmacy Bulk Packages, 1000 mL packaged 8 per case and 2000 mL packaged 4 per case.

NDC | REF | Size
0264-4500-05 | S4505 | 2000 mL
0264-4500-00 | S4500 | 1000 mL

Not made with natural rubber latex, DEHP or PVC.

Storage

Store in the closed corrugated case; do not expose solution to light until ready for use. Do not remove container from overwrap until ready to use. Do not use if overwrap has been opened or damaged. Exposure of pharmaceutical products to heat should be minimized. Avoid excessive heat. It is recommended that the product be stored at 20 to 25°C (68 to 77°F). [See USP Controlled Room Temperature.] Brief exposure to temperatures above 25°C during transport and storage will not adversely affect the product. Solution that has been frozen must not be used.

Rx only

Intralipid is a registered trademark of Fresenius Kabi AB.

Preparation Instructions for Plenamine™ 15% Bags for Direct Infusion

Caution: Plenamine™ 15% Pharmacy Bulk Package is not intended for direct intravenous administration.

The pharmacy bulk package is for use in a Pharmacy Admixture Service only. Use of this product is restricted to a suitable work area, such as a laminar flow hood (or an equivalent clean air compounding area).

Additives should not be made to Pharmacy Bulk Packages.

Designed for use with an unvented sterile dispensing set.

Step 1: Inspect Pharmacy Bulk Package overwrap and primary bag and do not use if damaged. Inspect oxygen indicator and do not use if oxygen indicator is pink or dark pink. Use only if container and seals are intact.

Step 2: To open, tear overwrap starting from the tear notches (Figure 1). Remove Plenamine™ 15% Pharmacy Bulk Package bag from overwrap and discard oxygen indicator, oxygen absorber and overwrap.

Step 3: Inspect Plenamine™ 15% Pharmacy Bulk Package bag visually (Figure 2). Parenteral drug products should be inspected visually for particulate matter and discoloration prior to administration, whenever solution and container permit. Inspect Plenamine™ 15% for cloudiness, haze or particulate matter in good lighting. Discard the bag if any particulates or discoloration are observed.

Step 4: Remove aluminum foil of outlet port at the bottom of the Pharmacy Bulk Package bag (Figure 3a) and attach an unvented sterile dispensing set (Figure 3b).

The container closure may be penetrated only one time, utilizing a suitable sterile dispensing set which allows measured dispensing of the contents.

The withdrawal of container contents should be accomplished without delay using aseptic technique. Discard container no later than 4 hours after initial closure puncture.

Use of a syringe with needle is not recommended. Multiple entries increase the potential of the microbial and particulate contamination.

B. Braun Medical Inc.
Bethlehem, PA 18018-3524 USA
1-800-227-2862
Made in Germany

Revised: October 2019

LD-537-2

PRINCIPAL DISPLAY PANEL - 1000 mL Bag Label

857/12624147/0118

NDC 0264-4500-00
REF S4500

LOT
EXP:
SN:

Plenamine™
15% Amino Acids Injection

1000 mL

PHARMACY BULK PACKAGE -
NOT FOR DIRECT INFUSION

Protect from light until use.
For Intravenous Use

Store at 20 to 25°C (68 to 77°F). [See USP
Controlled Room Temperature.] Solution that
has been frozen must not be used.
Do not expose to light before using. Once
closure is penetrated, transfer contents
promptly, total time not to exceed 4 hours.
See package insert for proper use of Pharmacy
Bulk Package.

Affix accompanying label
for date and time of entry

Each 100 mL contains:

Essential Amino Acids
Lysine (from Lysine Acetate, USP) | 1.18 g
Leucine, USP | 1.04 g
Phenylalanine, USP | 1.04 g
Valine, USP | 960 mg
Isoleucine, USP | 749 mg
Methionine, USP | 749 mg
Threonine, USP | 749 mg
Tryptophan, USP | 250 mg
Nonessential Amino Acids
Alanine, USP | 2.17 g
Arginine, USP | 1.47 g
Glycine, USP | 1.04 g
Histidine, USP | 894 mg
Proline, USP | 894 mg
Glutamic Acid | 749 mg
Serine, USP | 592 mg
Aspartic Acid, USP | 434 mg
Tyrosine, USP | 39 mg
Water for Injection USP | qs

pH 5.6 (5.2-6.0),
adjusted with acetic acid.

Acetate: 147.4 mEq/L, including quantity used
for pH adjustment.

Calculated Osmolarity: 1378 mOsmol/L
Contains no more than 25 mcg/L of aluminum.
Sterile, nonpyrogenic.

Single dose container. Use only if bag
and seal are undamaged and solution
is clear.
Do not remove container from overwrap
until ready for use. Do not use if
overwrap has been opened or damaged.
Administer intravenously.

Not made with natural rubber
latex, DEHP or PVC.

Rx only

B. Braun Medical Inc.
Bethlehem, PA 18018-3524 USA
1-800-227-2862
Made in Germany

LD-558-1

SET

PRINCIPAL DISPLAY PANEL - Accompanying 1000 mL and 2000 mL Bag Label

Date of Entry:___/____/_____

Time of Entry:____________________AM/PM

Discard______hours after initial entry

LD-585-2

0/12625337/1221

PRINCIPAL DISPLAY PANEL - 2000 mL Bag Label

857/12627286/0619

NDC 0264-4500-05
REF S4505

LOT
EXP:
SN:

Plenamine™
15% Amino Acids Injection

2000 mL

PHARMACY BULK PACKAGE -
NOT FOR DIRECT INFUSION

Protect from light until use.
For Intravenous Use

Store at 20 to 25°C (68 to 77°F). [See
USP Controlled Room Temperature.]
Solution that has been frozen must not
be used.
Do not expose to light before using. Once
closure is penetrated, transfer contents
promptly, total time not to exceed
4 hours.
See package insert for proper use of
Pharmacy Bulk Package.

Affix accompanying label
for date and time of entry

Each 100 mL contains:

Essential Amino Acids
Lysine (from Lysine Acetate, USP) | 1.18 g
Leucine, USP | 1.04 g
Phenylalanine, USP | 1.04 g
Valine, USP | 960 mg
Isoleucine, USP | 749 mg
Methionine, USP | 749 mg
Threonine, USP | 749 mg
Tryptophan, USP | 250 mg
Nonessential AminoAcids
Alanine, USP | 2.17 g
Arginine, USP | 1.47 g
Glycine, USP | 1.04 g
Histidine, USP | 894 mg
Proline, USP | 894 mg
Glutamic Acid | 749 mg
Serine, USP | 592 mg
Aspartic Acid, USP | 434 mg
Tyrosine, USP | 39 mg
Water for Injection USP | qs

pH 5.6 (5.2-6.0),
adjusted with acetic acid.

Acetate: 147.4 mEq/L, including quantity used
for pH adjustment.

Calculated Osmolarity: 1378 mOsmol/L
Contains no more than 25 mcg/L of
aluminum.

Sterile, nonpyrogenic. Single dose
container. Use only if bag and seal are
undamaged and solution is clear.
Do not remove container from overwrap
until ready to use. Do not use if
overwrap has been opened or damaged.
Administer intravenously.

Not made with natural rubber
latex, DEHP or PVC.

Rx only

B. Braun Medical Inc.
Bethlehem, PA 18018-3524 USA
1-800-227-2862
Made in Germany

LD-633-1

SET